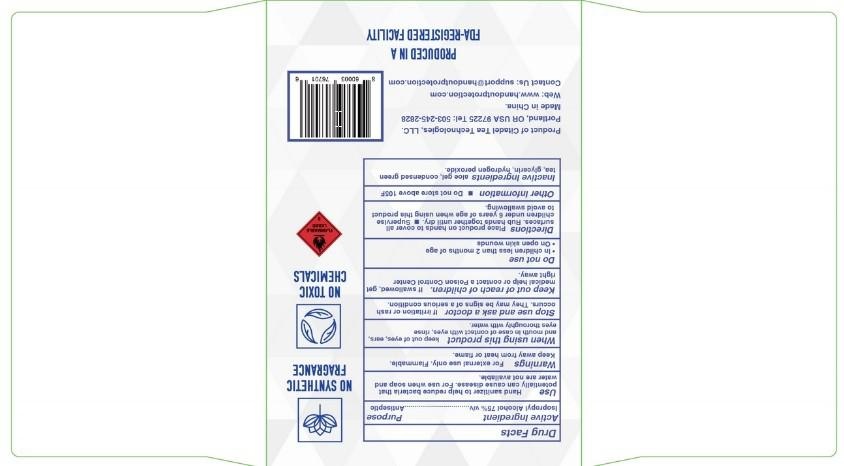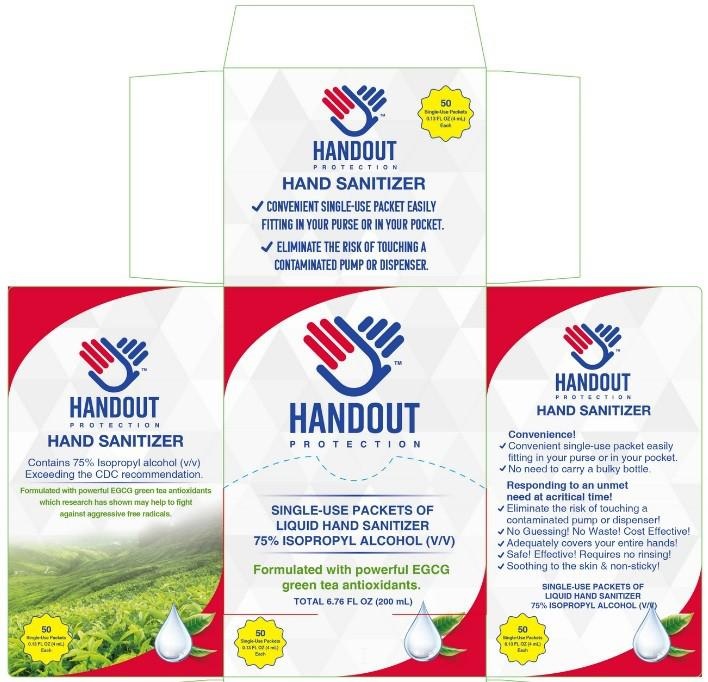 DRUG LABEL: HANDOUT PROTECTION HAND SANITIZER
NDC: 81820-001 | Form: LIQUID
Manufacturer: ZHEJIANG SAIRUI MEDICAL TECHNOLOGY CO., LTD.
Category: otc | Type: HUMAN OTC DRUG LABEL
Date: 20210325

ACTIVE INGREDIENTS: ISOPROPYL ALCOHOL 75 mL/100 mL
INACTIVE INGREDIENTS: ALOE VERA LEAF; HYDROGEN PEROXIDE; GLYCERIN; GREEN TEA LEAF

ACTIVE INGREDIENT

Isoproply Alcohol 75% v/v………………Antiseptic

KEEP OUT OF REACH OF CHILDREN

If swallowed, get medical help or contact a Poison Control Center right away.

DO NOT USE

- In children less than 2 months of age.
- On open skin wounds.

WARNINGS

For external use only. Flammable. Keep away from heat or flame.

PURPOSE

Hand sanitizer to help reduce bacteria that potentially can cause diseases. For use when soap and water are not available.

WHEN USING

Keep out of eyes, mouth in case of contact with eyes, ears and mouth. In case of contact with eyes, rinse eyes thoroughly with water.

DOSAGE AND ADMINISTRATION

Place product on hands to cover all surfaces. Rub hands together untill dry.

- Supervise children under 6 years of age when using this product to avoid swallowing.

INACTIVE INGREDIENT

aloe gel, condensed green tea, glycerine, hydrogen peroxide

STOP USE

If irritation or rash occurs. They may be signs of a serious condition.

INDICATIONS AND USAGE

Hand sanitizer to help reduce bacteria that potentially can cause diseases. For use when soap and water are not available.